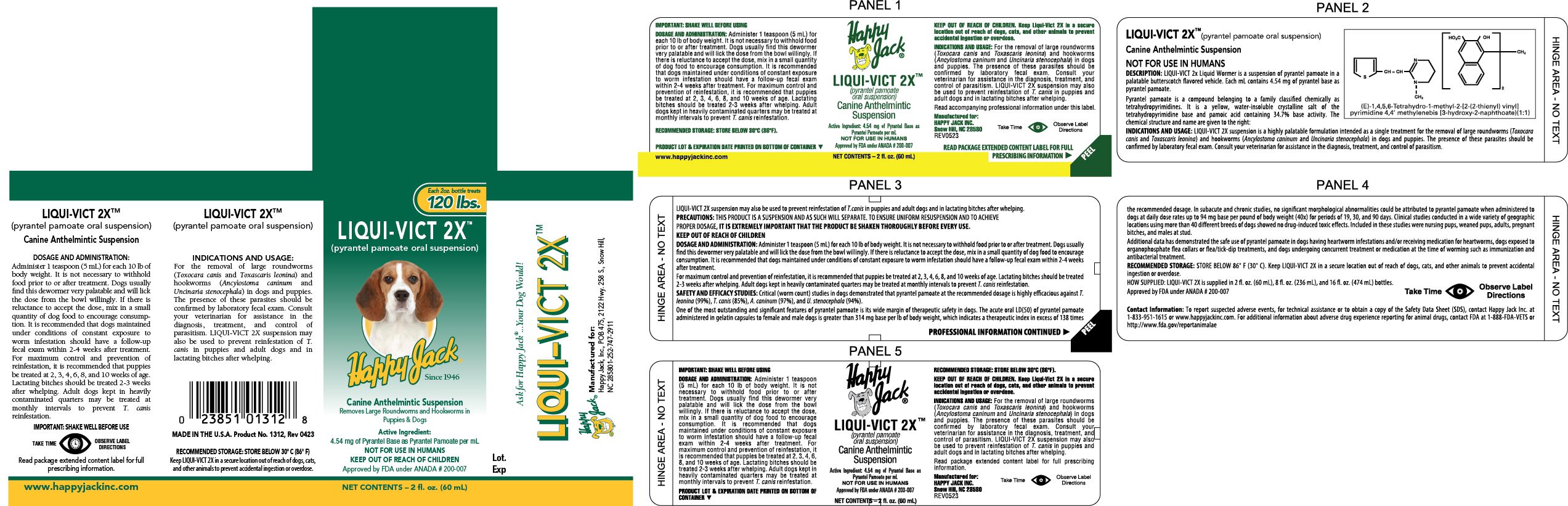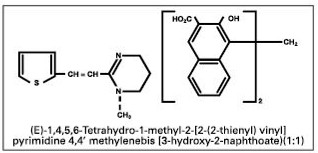 DRUG LABEL: Liqui-Vict 2X 
NDC: 23851-312 | Form: SUSPENSION
Manufacturer: Happy Jack Inc
Category: animal | Type: OTC ANIMAL DRUG LABEL
Date: 20260216

ACTIVE INGREDIENTS: pyrantel pamoate 4.54 mg/1 mL

Happy Jack®
LIQUI-VICT 2X™

Extended Content Label Panel 1

IMPORTANT: SHAKE WELL BEFORE USING

DOSAGE AND ADMINISTRATION: Administer 1 teaspoon (5 mL) for each 10 lb of body weight. It is not necessary to withhold food prior to or after treatment. Dogs usually find this dewormer very palatable and will lick the dose from the bowl willingly. If there is reluctance to accept the dose, mix in a small quantity of dog food to encourage consumption. It is recommended that dogs maintained under conditions of constant exposure to worm infestation should have a follow-up fecal exam within 2-4 weeks after treatment. For maximum control and prevention of reinfestation, it is recommended that puppies be treated at 2, 3, 4, 6, 8, and 10 weeks of age. Lactating bitches should be treated 2-3 weeks after whelping. Adult dogs kept in heavily contaminated quarters may be treated at monthly intervals to prevent T. canis reinfestation.

RECOMMENDED STORAGE: STORE BELOW 30°C (86°F).

PRODUCT LOT & EXPIRATION DATE PRINTED ON BOTTOM OF CONTAINER

www.happyjackinc.com

Happy Jack(R)

LIQUI-VICT 2XTM

(pyrantel pamoate oral suspension)

Canine Anthelmintic Suspension

Active Ingredient: 4.54 mg of Pyrantel Base as

Pyrantel Pamoate per mL

NOT FOR USE IN HUMANS

Approved by FDA under ANADA #200-007

NET CONTENTS – 2 fl. oz. (60 mL)

KEEP OUT OF REACH OF CHILDREN. Keep Liqui-Vict 2X in a secure
location out of reach of dogs, cats, and other animals to prevent
accidental ingestion or overdose.

INDICATIONS AND USAGE: For the removal of large roundworms
(Toxocara canis and Toxascaris leonina) and hookworms
(Ancylostoma caninum and Uncinaria stenocephala) in dogs
and puppies. The presence of these parasites should be
confirmed by laboratory fecal exam. Consult your
veterinarian for assistance in the diagnosis, treatment, and
control of parasitism. LIQUI-VICT 2X suspension may also
be used to prevent reinfestation of T. canis in puppies and
adult dogs and in lactating bitches after whelping.
Read accompanying professional information under this label.

Manufactured for:
HAPPY JACK INC.
Snow Hill, NC 28580REV0523

Take Time

(Eye Symbol)

Observe Label Directions

READ PACKAGE EXTENDED CONTENT LABEL FOR FULL PRESCRIBING INFORMATION

(PEEL)

Extended Content Label Panel 2

LIQUI-VICT 2XTM (pyrantel pamoate oral suspension)

Canine Anthelmintic Suspension

NOT FOR USE IN HUMANS

DESCRIPTION: LIQUI-VICT 2x Liquid Wormer is a suspension of pyrantel pamoate in a palatable butterscotch flavored vehicle. Each mL contains 4.54 mg of pyrantel base as pyrantel pamoate.

Pyrantel pamoate is a compound belonging to a family classified chemically as tetrahydropyrimidines. It is a yellow, water-insoluble crystalline salt of the tetrahydropyrimidine base and pamoic acid containing 34.7% base activity. The chemical structure and name are given to the right:

(E)-1,4,5,6-Tetrahydro-1-methyl-2-[2-(2-thienyl) vinyl] pyrimidine 4,4' methylenebis [3-hydroxy-2-naphthoate)(1 :1)

INDICATIONS AND USAGE: LIQUI-VICT 2X suspension is a highly palatable formulation intended as a single treatment for the removal of large roundworms (Toxocara canis and Toxascaris leonina) and hookworms (Ancylostoma caninum and Uncinaria stenocephala) in dogs and puppies. The presence of these parasites should be confirmed by laboratory fecal exam. Consult your veterinarian for assistance in the diagnosis, treatment, and control of parasitism.

Extended Content Label Panel 3

LIQUI-VICT 2X suspension may also be used to prevent reinfestation of T. canis in puppies and adult dogs and in lactating bitches after whelping.

PRECAUTIONS: THIS PRODUCT IS A SUSPENSION AND AS SUCH WILL SEPARATE. TO ENSURE UNIFORM RESUSPENSION AND TO ACHIEVE
PROPER DOSAGE, IT IS EXTREMELY IMPORTANT THAT THE PRODUCT BE SHAKEN THOROUGHLY BEFORE EVERY USE.

KEEP OUT OF REACH OF CHILDREN

DOSAGE AND ADMINISTRATION: Administer 1 teaspoon (5 mL) for each 10 lb of bodyweight. It is not necessary to withhold food prior to or after treatment. Dogs usually find this dewormer very palatable and will lick the dose from the bowl willingly. If there is reluctance to accept the dose, mix in a small quantity of dog food to encourage consumption. It is recommended that dogs maintained under conditions of constant exposure to worm infestation should have a follow-up fecal exam within 2-4 weeks after treatment.

For maximum control and prevention of reinfestation, it is recommended that puppies be treated at 2, 3, 4, 6, 8, and 10 weeks of age. Lactating bitches should be treated 2-3 weeks after whelping. Adult dogs kept in heavily contaminated quarters may be treated at monthly intervals to prevent T. canis reinfestation.

SAFETY AND EFFICACY STUDIES: Critical (worm count) studies in dogs demonstrated that pyrantel pamoate at the recommended dosage is highly efficacious against T. leonina (99%), T. canis (85%), A. caninum (97%), and U. stenocephala (94%).

One of the most outstanding and significant features of pyrantel pamoate is its wide margin of therapeutic safety in dogs. The acute oral LD(50) of pyrantel pamoate administered in gelatin capsules to female and male dogs is greater than 314 mg base per lb of body weight, which indicates a therapeutic index in excess of 138 times

PROFESSIONAL INFORMATION CONTINUED

Extended Content Label Panel 4

the recommended dosage. In subacute and chronic studies, no significant morphological abnormalities could be attributed to pyrantel pamoate when administered to dogs at daily dose rates up to 94 mg base per pound of body weight (40x) for periods of 19, 30, and 90 days. Clinical studies conducted in a wide variety of geographic locations using more than 40 different breeds of dogs showed no drug-induced toxic effects. Included in these studies were nursing pups, weaned pups, adults, pregnant bitches, and males at stud.

Additional data has demonstrated the safe use of pyrantel pamoate in dogs having heartworm infestations and/or receiving medication for heartworms, dogs exposed to organophosphate flea collars or flea/tick-dip treatments, and dogs undergoing concurrent treatment or medication at the time of worming such as immunization and antibacterial treatment.

RECOMMENDED STORAGE: STORE BELOW 86° F (30° C). Keep LIQUI-VICT 2X in a secure location out of reach of dogs, cats, and other animals to prevent accidental ingestion or overdose.

HOW SUPPLIED: LIQUI-VICT 2X is supplied in 2 fl. oz. (60 mL), 8 fl. oz. (236 mL), and 16 fl. oz. (474 mL) bottles.

Approved by FDA under ANADA # 200-007

Take Time

(Eye Symbol)

Observe Label Directions

Contact Information: To report suspected adverse events, for technical assistance or to obtain a copy of the Safety Data Sheet (SDS), contact Happy Jack Inc. at 1-800-326-5225 or www.happyjackinc.com. For additional information about adverse drug experience reporting for animal drugs, contact FDA at 1-888-FDA-VETS or http://www.fda.gov/reportanimalae

Extended Content Label Panel 5 (Bottom Ply)

IMPORTANT: SHAKE WELL BEFORE USING

DOSAGE AND ADMINISTRATION: Administer 1 teaspoon
(5 ml) for each 10 lb of body weight. It is not
necessary to withhold food prior to or after
treatment. Dogs usually find this dewormer very
palatable and will lick the dose from the bowl
willingly. If there is reluctance to accept the dose,
mix in a small quantity of dog food to encourage
consumption. It is recommended that dogs
maintained under conditions of constant exposure
to worm infestation should have a follow-up fecal
exam within 2-4 weeks after treatment. For
maximum control and prevention of reinfestation, it
is recommended that puppies be treated at 2, 3, 4, 6,
8, and 10 weeks of age. Lactating bitches should be
treated 2-3 weeks after whelping. Adult dogs kept in
heavily contaminated quarters may be treated at
monthly intervals to prevent T. canis reinfestation.
PROOUCT LOT & EXPIRATION DATE PRINTED ON BOTTOM OF CONTAINER

HAPPY JACK

LIQUI-VICT 2XTM

(pyrantel pamoate oral suspension)

Canine Anthelmintic Suspension

Active Ingredient: 4.54 mg of Pyrantel Base as

Pyrantel Pamoate per mL

NOT FOR USE IN HUMANS

Approved by FDA under ANADA #200-007

NET CONTENTS – 2 fl. oz. (60 mL)

RECOMMENDED STORAGE: STORE BELOW 30°C (86°F)

KEEP OUT OF REACH OF CHILDREN. Keep Liqui-Vict 2X in a secure
location out of reach of dogs, cats, and other animals to prevent
accidental ingestion or overdose.

INDICATIONS AND USAGE: For the removal of large roundworms
(Toxocara canis and Toxascaris leonina) and hookworms
(Ancylostoma caninum and Uncinaria stenocephala) in dogs
and puppies. The presence of these parasites should be
confirmed by laboratory fecal exam. Consult your
veterinarian for assistance in the diagnosis, treatment, and
control of parasitism. LIQUI-VICT 2X suspension may also
be used to prevent reinfestation of T. canis in puppies and
adult dogs and in lactating bitches after whelping.

Read package extended content label for full prescribing information.

Manufactured for:
HAPPY JACK, INC.
Snow Hill, NC 28580

REV0523

Take Time
(Eye Symbol)
Observe Label
Directions

PRINCIPAL DISPLAY PANEL - 60 mL Bottle Label

Happy Jack

LIQUI-VICT 2X

(pyrantel pamoate)

Canine Anthelmintic Suspension

Active Ingredient:

4.54 mg of pyrantel base

as pyrantel pamoate per ml.

FOR ANIMAL USE ONLY

ANADA 200-007 Approved by FDA

NET CONTENTS – 2 FL. OZ. (60ML)